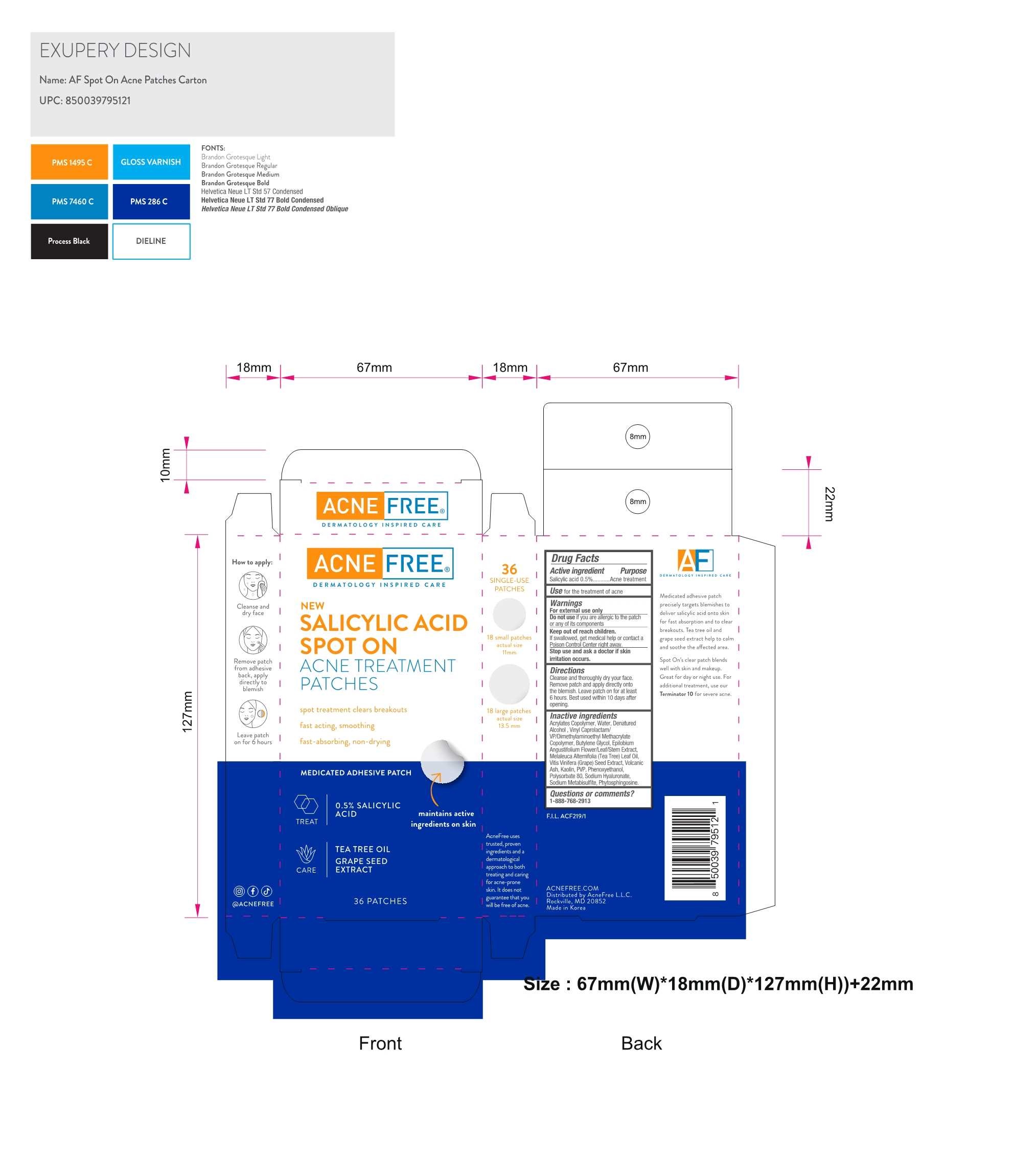 DRUG LABEL: Spot On Acne Patch
NDC: 80861-111 | Form: PATCH
Manufacturer: ACNEFREE, LLC
Category: otc | Type: HUMAN OTC DRUG LABEL
Date: 20240618

ACTIVE INGREDIENTS: SALICYLIC ACID 1.24 g/1 1
INACTIVE INGREDIENTS: WATER; TEA TREE OIL; HYALURONIC ACID

USE

for treatment of acne

WARNINGS

For external use only

Do not use if you are allergic to the patch or any of its components

Keep out of reach of children.

If swallowed, get medical help or contact a Poison Control Center right away.

Stop use

Stop use and ask a doctor if skin irritation occurs.

Directions

Cleanse and thoroughly dry your face. Remove patch adn apply directly onto the blemish. Leave patch on for at least 6 hours. Best used within 10 days after opening.

Inactive Ingredients

Acrylates Copolymer, Water, Denatured Alcohol , Vinyl Caprolactam/ VP/Dimethylaminoethyl Methacrylate Copolymer, Butylene Glycol, Epilobium Angustifolium Flower/Leaf/Stem Extract, Melaleuca Alternifolia (Tea Tree) Leaf Oil, Vitis Vinifera (Grape) Seed Extract, Volcanic Ash, Kaolin, PVP, Phenoxyethanol, Polysorbate 80, Sodium Hyaluronate, Sodium Metabisulfite, Phytosphingosine.